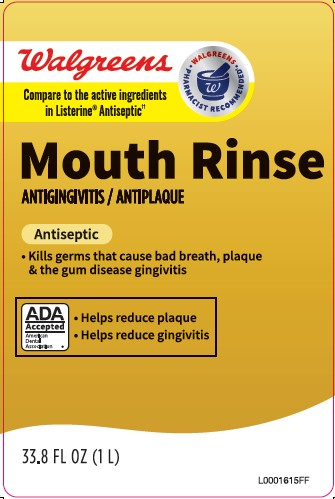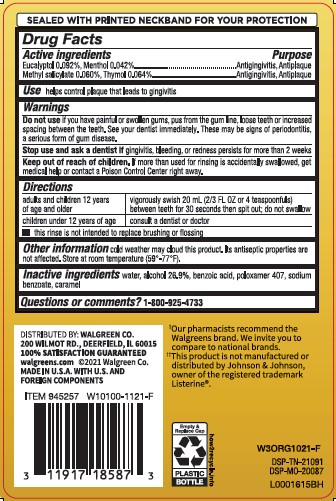 DRUG LABEL: Rinse
NDC: 0363-0318 | Form: MOUTHWASH
Manufacturer: Walgreen Co.
Category: otc | Type: HUMAN OTC DRUG LABEL
Date: 20260212

ACTIVE INGREDIENTS: EUCALYPTOL 0.92 mg/1 mL; MENTHOL 0.42 mg/1 mL; METHYL SALICYLATE 0.6 mg/1 mL; THYMOL 0.64 mg/1 mL
INACTIVE INGREDIENTS: WATER; ALCOHOL; BENZOIC ACID; POLOXAMER 407; SODIUM BENZOATE; CARAMEL

Walgreens 318.003/318AH-318AI
Antiseptic Mouthrinse

Tamper Evident Statement

SEALED WITH PRINTED NECKBAND FOR YOUR PROTECTION

Active ingredients

Eucalyptol 0.092%

Menthol 0.042%

Methyl salicylate 0.060%

Thymol 0.064%

Purpose

Antigingivitis, Antiplaque

Use

helps control plaque that leads to gingivitis

Warnings

for this product

Do not use

if you have painful or swollen gums, pus from the gum line, loose teeth or increased spacing between the teeth. See your dentist immediately.

These may be signs of periodontitis, a serious form of gum disease.

Stop use and ask a dentist if

gingivitis, bleeding, or redness persists for more thatn 2 weeks

Keep out of reach of children

If more than used for rinsing is accidentally swallowed, get medical help or contact a Poison Control Center right away.

Directions

adults and children 12 years of age and older - vigorously swish 20 mL (2/3 FL OZ or 4 teaspoonsfuls) between teeth for 30 seconds then spit out; do not swallow

children under 12 years of age - consult a dentist or doctor

- this rinse is not intended to replace brushing or flossing

Other information

cold weather may cloud this product. Its antiseptic properties are not affected. Store at room temperature (59°-77°F).

Inactive ingredients

water, alcohol 26.9%, benzoic acid, poloxamer 407, sodium benzoate, caramel

Questions or comments?

1-800-925-4733

Adverse Reactions

DISTRIUBTED BY: WALGREEN CO.

200 WILMOT RD., DEERFIELD, IL 60015

100% SATISFACTION GUARANTEED

walgreens.com ©2021 Walgreen Co.

MADE IN U.S.A. WITH U.S. AD FOREIGN COMPONENTS

†Our pharmacist recommend the Walgreens brand. We invite you to compare to national brands.

††This product is not manufactured or distributed by Johnson & Johnson, owner of the registered trademark Listerine®.

Empty & Replace Cap

PLASTIC BOTTLE

how2recycle.info

DSP-TN-21091

DSP-MO-20087

Principal display panel

Walgreens

WALGREENS - PHARMACIST RECOMMENDED†

Compare to the active ingredients in Listerine®Antiseptic††

Mouth Rinse

ANTIGINGIVITIS/ANTIPLAQUE

Antiseptic

- Kills germs that cause bad breath, plaque & the gum disease gingivitis

ADA Accepted

American Dental Association

- Helps reduce plaque
- Helps reduce gingivitis

33.8 FL OZ (1 L)